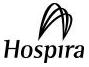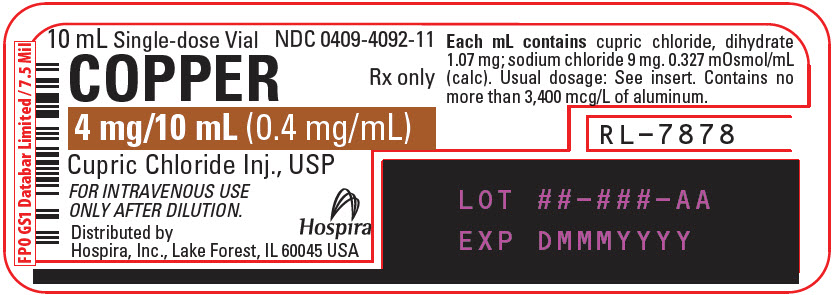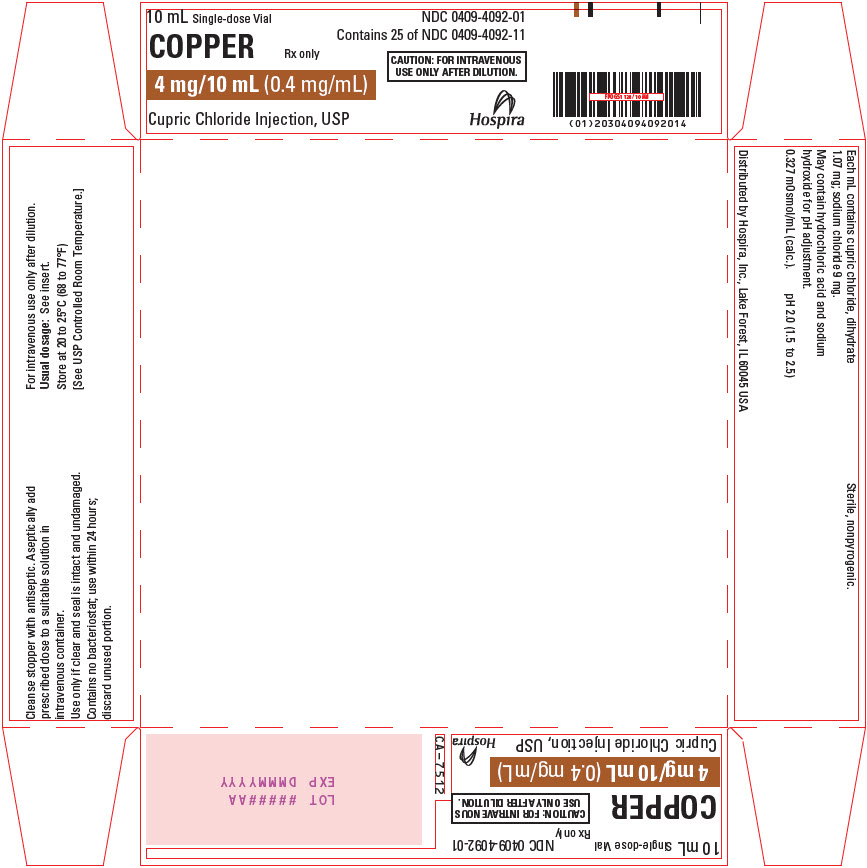 DRUG LABEL: COPPER
NDC: 0409-4092 | Form: INJECTION, SOLUTION
Manufacturer: Hospira, Inc.
Category: prescription | Type: HUMAN PRESCRIPTION DRUG LABEL
Date: 20250623

ACTIVE INGREDIENTS: CUPRIC CHLORIDE 0.4 mg/1 mL
INACTIVE INGREDIENTS: SODIUM CHLORIDE 9 mg/1 mL; HYDROCHLORIC ACID; SODIUM HYDROXIDE; WATER

COPPER
0.4 mg/mL

Cupric Chloride

Injection, USP

FOR I.V. USE ONLY AFTER DILUTION

Plastic Vial Rx only

DESCRIPTION

Copper (Cupric Chloride Injection, USP) 0.4 mg/mL is a sterile, nonpyrogenic solution intended for use as an additive to intravenous solutions for total parenteral nutrition (TPN). Each mL of solution contains 1.07 mg cupric chloride, dihydrate and 9 mg sodium chloride.

The solution contains no bacteriostat, antimicrobial agent or added buffer. The pH is 2.0 (1.5 to 2.5); product may contain hydrochloric acid and sodium hydroxide for pH adjustment. The osmolarity is 0.327 mOsmol/mL (calc.).

Cupric chloride, USP is chemically designated cupric chloride, dihydrate (CuCl2 • 2H2O), a crystalline compound freely soluble in water.

Sodium Chloride, USP is chemically designated NaCl, a white crystalline compound freely soluble in water.

The semi-rigid vial is fabricated from a specially formulated polyolefin. It is a copolymer of ethylene and propylene. The safety of the plastic has been confirmed by tests in animals according to USP biological standards for plastic containers. The small amount of water vapor that can pass through the plastic container wall will not significantly alter the drug concentration.

CLINICAL PHARMACOLOGY

Copper is an essential nutrient which serves as a cofactor for serum ceruloplasmin, an oxidase necessary for proper formation of the iron carrier protein, transferrin. Copper also helps maintain normal rates of red and white blood cell formation.

Providing copper during TPN helps prevent development of the following deficiency symptoms: Leukopenia, neutropenia, anemia, depressed ceruloplasmin levels, impaired transferrin formation, secondary iron deficiency and osteoporosis.

Normal serum copper values range from 80 to 163 mcg/dl (mean, approximately 110 mcg/dl). The serum copper level at which deficiency symptoms appear is not precisely defined.

In the plasma, about 7% of copper is bound to albumin and amino acids. In the liver, about 93% of copper is bound to ceruloplasmin and released to the serum. The daily turnover of copper through ceruloplasmin is approximately 0.5 mg. Copper is primarily excreted through the bile and into the gastrointestinal tract where it is not reabsorbed. Copper is also eliminated through the kidneys.

INDICATIONS AND USAGE

Copper (Cupric Chloride Injection) is indicated for use as a supplement to intravenous solutions given for TPN. Administration helps to maintain copper serum levels and to prevent depletion of endogenous stores and subsequent deficiency symptoms.

CONTRAINDICATIONS

Copper (Cupric Chloride Injection) is contraindicated in patients with hypersensitivity to copper (see WARNINGS: Hypersensitivity Reactions).

WARNINGS

Hepatic Accumulation

Copper is primarily eliminated in the bile and excretion is decreased in patients with cholestasis and/or cirrhosis. Hepatic accumulation of copper has been reported in autopsies of patients receiving long-term parenteral nutrition containing copper at dosages higher than recommended.

Administration of copper to patients with cholestasis and/or cirrhosis may cause hepatic accumulation of copper. Administration of copper to patients with Wilson disease, an inborn error of copper metabolism with a defect in hepatocellular copper transport, may cause both increased hepatic accumulation of copper and aggravation of the underlying hepatocellular degeneration.

For patients with cholestasis, biliary dysfunction, or cirrhosis, monitor hepatic and biliary function during long-term administration of Cupric Chloride Injection. If a patient develops signs or symptoms of hepatobiliary disease during the use of Cupric Chloride Injection, obtain serum concentrations of copper and ceruloplasmin, and adjust the dose as indicated (see PRECAUTIONS: Hepatic Impairment).

Hypersensitivity Reactions

Postmarket safety reporting has identified copper hypersensitivity in women receiving copper-containing intrauterine devices, providing evidence that patients may experience hypersensitivity reactions when exposed to this metal. If hypersensitivity reactions (e.g., pruritis, angioedema, dyspnea, rash, urticaria) occur in patients receiving Cupric Chloride Injection in parenteral nutrition, discontinue the product, and initiate appropriate medical treatment (see CONTRAINDICATIONS).

Aluminum Toxicity

This product contains aluminum that may be toxic. Aluminum may reach toxic levels with prolonged parenteral administration if kidney function is impaired. Premature neonates are particularly at risk because their kidneys are immature, and they require large amounts of calcium and phosphate solutions, which contain aluminum.

Research indicates that patients with impaired kidney function, including premature neonates, who receive parenteral levels of aluminum at greater than 4 to 5 mcg/kg/day accumulate aluminum at levels associated with central nervous system and bone toxicity. Tissue loading may occur at even lower rates of administration.

PRECAUTIONS

Laboratory Tests

Twice monthly serum assays for copper and/or ceruloplasmin are suggested for monitoring copper concentrations in long-term TPN patients. As ceruloplasmin is a cuproenzyme, ceruloplasmin assays may be depressed secondary to copper deficiency.

Carcinogenesis, Mutagenesis, and Impairment of Fertility

Long-term animal studies to evaluate the carcinogenic potential of Copper 0.4 mg/mL (Cupric Chloride Injection) have not been performed, nor have studies been done to assess mutagenesis or impairment of fertility.

Nursing Mothers

It is not known whether this drug is excreted in human milk. Because many drugs are excreted in human milk, caution should be exercised when Copper 0.4 mg/mL (Cupric Chloride Injection) is administered to a nursing woman.

Pediatric Use

The safety and effectiveness of Cupric Chloride Injection have been established in pediatric patients receiving parenteral nutrition (see DOSAGE AND ADMINISTRATION).

Pregnancy

Animal reproduction studies have not been conducted with cupric chloride. It is also not known whether cupric chloride can cause fetal harm when administered to a pregnant woman or can affect reproductive capacity. Cupric chloride should be given to a pregnant woman only if clearly indicated.

Geriatric Use

An evaluation of current literature revealed no clinical experience identifying differences in response between elderly and younger patients. In general, dose selection for an elderly patient should be cautious, usually starting at the low end of the dosing range, reflecting the greater frequency of decreased hepatic, renal, or cardiac function, and of concomitant disease or other drug therapy.

Hepatic Impairment

Copper is primarily excreted in the bile. Excretion is decreased in patients with cholestasis and/or cirrhosis (see CLINICAL PHARMACOLOGY). Hepatic accumulation of copper has been reported with long-term administration of parenteral nutrition at dosages higher than recommended (see WARNINGS: Hepatic Accumulation). For patients with cholestasis or cirrhosis, monitor hepatic and biliary function during long-term administration of Cupric Chloride Injection. If a patient develops signs or symptoms of hepatobiliary disease during use of Cupric Chloride Injection, obtain serum concentrations of copper and ceruloplasmin.

ADVERSE REACTIONS

None known.

DRUG ABUSE AND DEPENDENCE

None known.

OVERDOSAGE

Acute copper toxicity has been reported in patients with oral, intravenous, or subcutaneous administration. Clinical manifestations included metallic taste, nausea, vomiting, diarrhea, abdominal pain, neurological signs, such as encephalopathy, and multi-organ failure involving kidney, liver, blood, and cardiovascular systems, which may be fatal. Chelating agents, such as D-penicillamine, can be used for treatment of acute toxicity. Long-term administration of parenteral copper above the recommended dosage may result in significant accumulation of copper in the liver, brain, and other tissues with possible organ damage (see WARNINGS: Hepatic Accumulation).

DOSAGE AND ADMINISTRATION

- Copper (Cupric Chloride Injection) contains 0.4 mg of copper per mL and is administered intravenously only after dilution. The additive should be diluted in a volume of fluid not less than 100 mL.
- For the adult receiving TPN, the suggested additive dosage of copper is 0.3 to 0.5 mg/day.
- For pediatric patients, the suggested additive dosage of copper is 20 mcg/kg/day (0.05 mL/kg/day) up to a maximum of 500 mcg/day.
- This product is not appropriate for patients weighing less than 4 kg due to the inability to measure the appropriate amount of the product.
- Do not administer Copper (Cupric Chloride Injection) intramuscularly because the acidic pH of the solution may cause considerable tissue irritation.

Copper (Cupric Chloride Injection) should only be used in conjunction with a pharmacy directed admixture program using aseptic technique in a laminar flow environment; it should be used promptly and in a single operation without any repeated penetrations. The solution contains no preservatives; discard the unused portion immediately after the admixture procedure is completed.

Copper (Cupric Chloride Injection) should be inspected visually for particulate matter and discoloration prior to administration. Do not use unless the solution is clear, and the seal is intact.

Cupric ion may degrade ascorbic acid in TPN solutions. In order to avoid this loss of ascorbate, multivitamin additives should be added to TPN solutions immediately prior to infusion. Alternatively, the multivitamin additive may be added to one container of TPN solution, followed by copper in a subsequent container.

HOW SUPPLIED

Copper 0.4 mg/mL (Cupric Chloride Injection, USP) is supplied as follows:

Unit of Sale | Concentration
NDC 0409-4092-01 Tray containing 25 - 10 mL Single-dose Plastic Vials | 4 mg/10 mL (0.4 mg/mL)

Store at 20 to 25°C (68 to 77°F). [See USP Controlled Room Temperature.]

Distributed by Hospira, Inc., Lake Forest, IL 60045 USA

LAB-1067-3.0

Revised: 06/2025

PRINCIPAL DISPLAY PANEL - 10 mL Vial Label

10 mL Single-dose Vial
NDC 0409-4092-11

COPPER
Rx only

4 mg/10 mL (0.4 mg/mL)

Cupric Chloride Inj., USP

FOR INTRAVENOUS USE
ONLY AFTER DILUTION.

Distributed by
Hospira, Inc., Lake Forest, IL 60045 USA

Hospira

PRINCIPAL DISPLAY PANEL - 10 mL Vial Tray

10 mL Single-dose Vial
NDC 0409-4092-01
Contains 25 of NDC 0409-4092-11

COPPER
Rx only

4 mg/10 mL (0.4 mg/mL)

CAUTION: FOR INTRAVENOUS
USE ONLY AFTER DILUTION.

Cupric Chloride Injection, USP

Hospira